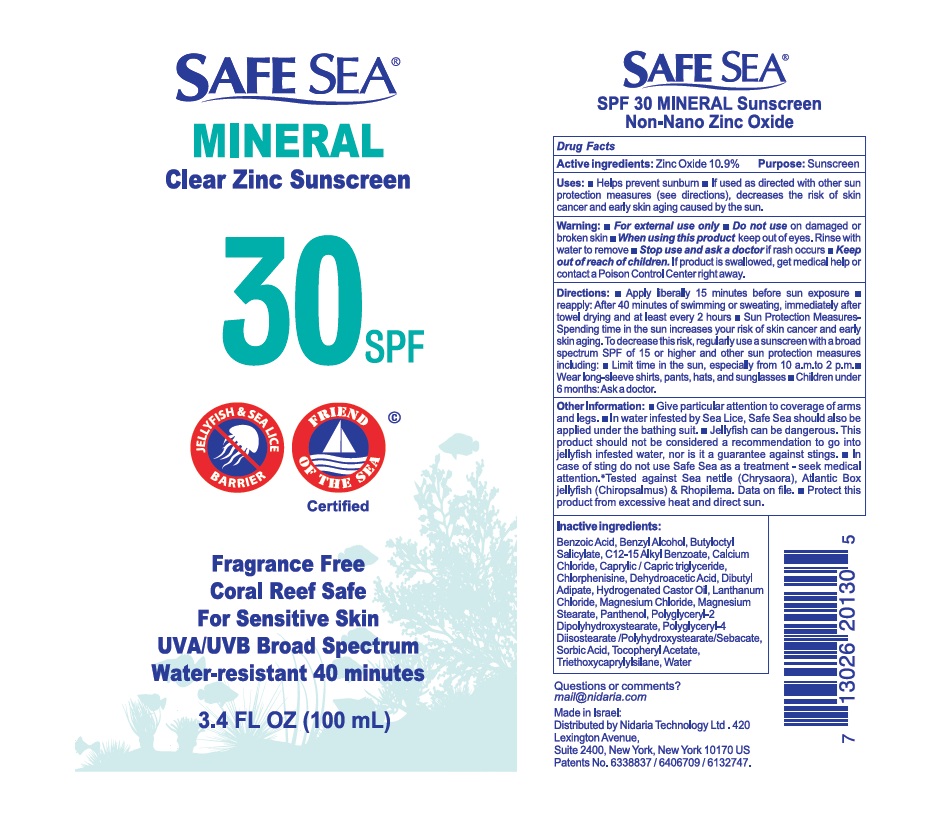 DRUG LABEL: Safe Sea SPF 30
NDC: 65435-0600 | Form: LOTION
Manufacturer: Nidaria Technology Ltd.
Category: otc | Type: HUMAN OTC DRUG LABEL
Date: 20251124

ACTIVE INGREDIENTS: ZINC OXIDE 10.9 g/100 g
INACTIVE INGREDIENTS: MEDIUM-CHAIN TRIGLYCERIDES; ALKYL (C12-15) BENZOATE; DIBUTYL ADIPATE; BUTYLOCTYL SALICYLATE; POLYGLYCERYL-2 DIPOLYHYDROXYSTEARATE; TRIETHOXYCAPRYLYLSILANE; POLYGLYCERYL-4 DIISOSTEARATE/POLYHYDROXYSTEARATE/SEBACATE; MAGNESIUM STEARATE; HYDROGENATED CASTOR OIL; PANTHENOL; .ALPHA.-TOCOPHEROL ACETATE; LANTHANUM CHLORIDE; MAGNESIUM CHLORIDE; CALCIUM CHLORIDE; BENZYL ALCOHOL; CHLORPHENESIN; BENZOIC ACID; SORBIC ACID; DEHYDROACETIC ACID; WATER

Drug Facts

Active ingredient

Zinc Oxide 10.9%

Purpose

Sunscreen

Uses

- Helps prevent sunburn
- If used as direacted with other sun protection measures (see directions), decreases the risk of skin cancer and early aging skin caused by the sun

Warnings

- For external use only
- Do not use on damagedor broken skin
- When using this productkeep out of eyes. Rinse with water to remove
- Stop use and ask a doctorif rash occurs
- Keep out of reach of children. If product is swallowed, get medical help or contact a Poison Control Center right away.

Directions

- Apply liberally 15 minutes before sun exposure
- reapply: After 40 minutes of swimming or sweating, immediately after towel drying and at least every 2 hours
- Sun Protection MeasuresSpending time in the sun increases your risk of skin cancer and early skin aging. To decrease this risk, regularly use a sunscreen with a broad spectrum SPF of 15 or higher and other sun protection measures including:
- Limit time in the sun, especially from 10 a.m.to 2 p.m.
- Wear long-sleeve shirts, pants, hats, and sunglasses
- Children under 6 months: Ask a doctor.

Other Information

- Give particular attention to coverage of arms and legs.
- In water infested by Sea Lice, Safe Sea should also be applied under the bathing suit.
- Jellyfish can be dangerous. This product should not be considered a recommendation to go into jellyfish infested water, nor is it a guarantee against stings.
- In case of sting do not use Safe Sea as a treatment - seek medical attention.*Tested against Sea nettle (Chrysaora), Atlantic Box jellyfish (Chiropsalmus) & Rhopilema. Data on file.
- Protect this product from excessive heat and direct sun.

Inactive ingredients

Benzoic Acid, Benzyl Alcohol, Butyloctyl Salicylate, C12-15 Alkyl Benzoate, Calcium Chloride, Caprylic / Capric triglyceride, Chlorphenisine, Dehydroacetic Acid, Dibutyl Adipate, Hydrogenated Castor Oil, Lanthanum Chloride, Magnesium Chloride, Magnesium Stearate, Panthenol, Polyglyceryl-2 Dipolyhydroxystearate, Polyglyceryl-4 Diisostearate /Polyhydroxystearate/Sebacate, Sorbic Acid, Tocopheryl Acetate, Triethoxycaprylylsilane, Water